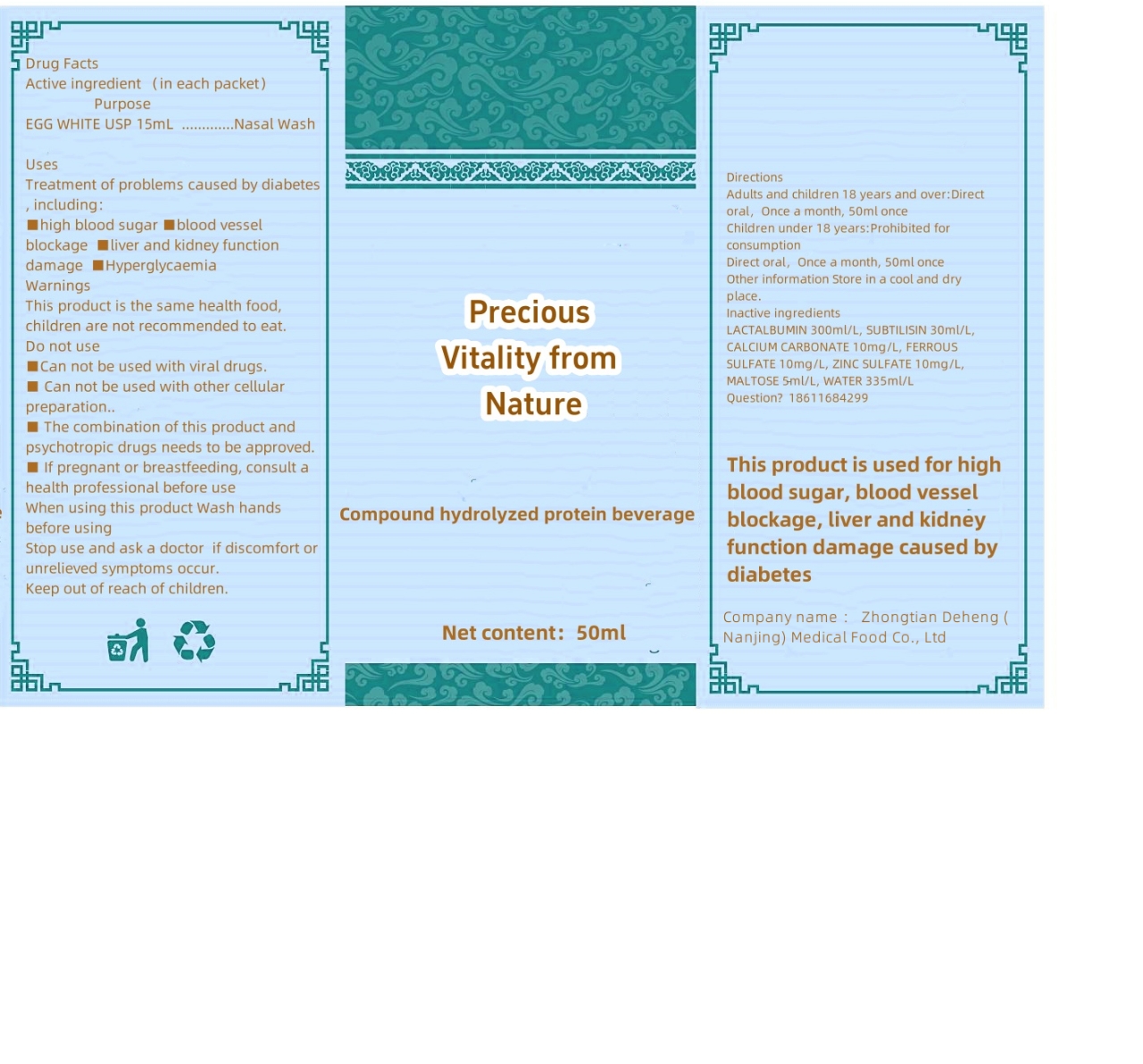 DRUG LABEL: Compound hydrolyzed protein beverage
NDC: 85005-001 | Form: LIQUID
Manufacturer: Nanjing Zhongtiandeheng Applied Stemmedical Co., Ltd
Category: otc | Type: HUMAN OTC DRUG LABEL
Date: 20241213

ACTIVE INGREDIENTS: EGG WHITE 6 g/100 mL
INACTIVE INGREDIENTS: MALTOSE; FERROUS SULFATE; .ALPHA.-LACTALBUMIN; ZINC SULFATE; WATER; CALCIUM CARBONATE; SUBTILISIN

85005-001-01

Active ingredient

Egg White 3g

Purpose

Blood vessels health care

Uses

Treatment of problems caused by diabetes, including：
■high blood sugar ■blood vessel blockage ■liver and kidney function damage ■Hyperglycaemia

Warnings

This product is the same health food, children are not recommended to eat.

Do not use

■ Can not be used with viral drugs.

■ Can not be used with other cellular preparation..

■ The combination of this product and psychotropic drugs needs to be approved.

■ If pregnant or breastfeeding, consult a health professional before use

When using this product

Wash hands before using

Stop use and ask a doctor

if discomfort or unrelieved symptoms occur.

Directions

Adults and children 18 years and over: Direct oral, Once a month, 50ml once
Children under 18 years: Prohibited for consumption
Direct oral, Once a month, 50ml once

Inactive ingredients

CALCIUM CARBONATE, FERROUS SULFATE, LACTALBUMIN, MALTOSE, SUBTILISIN, WATER, ZINC SULFATE